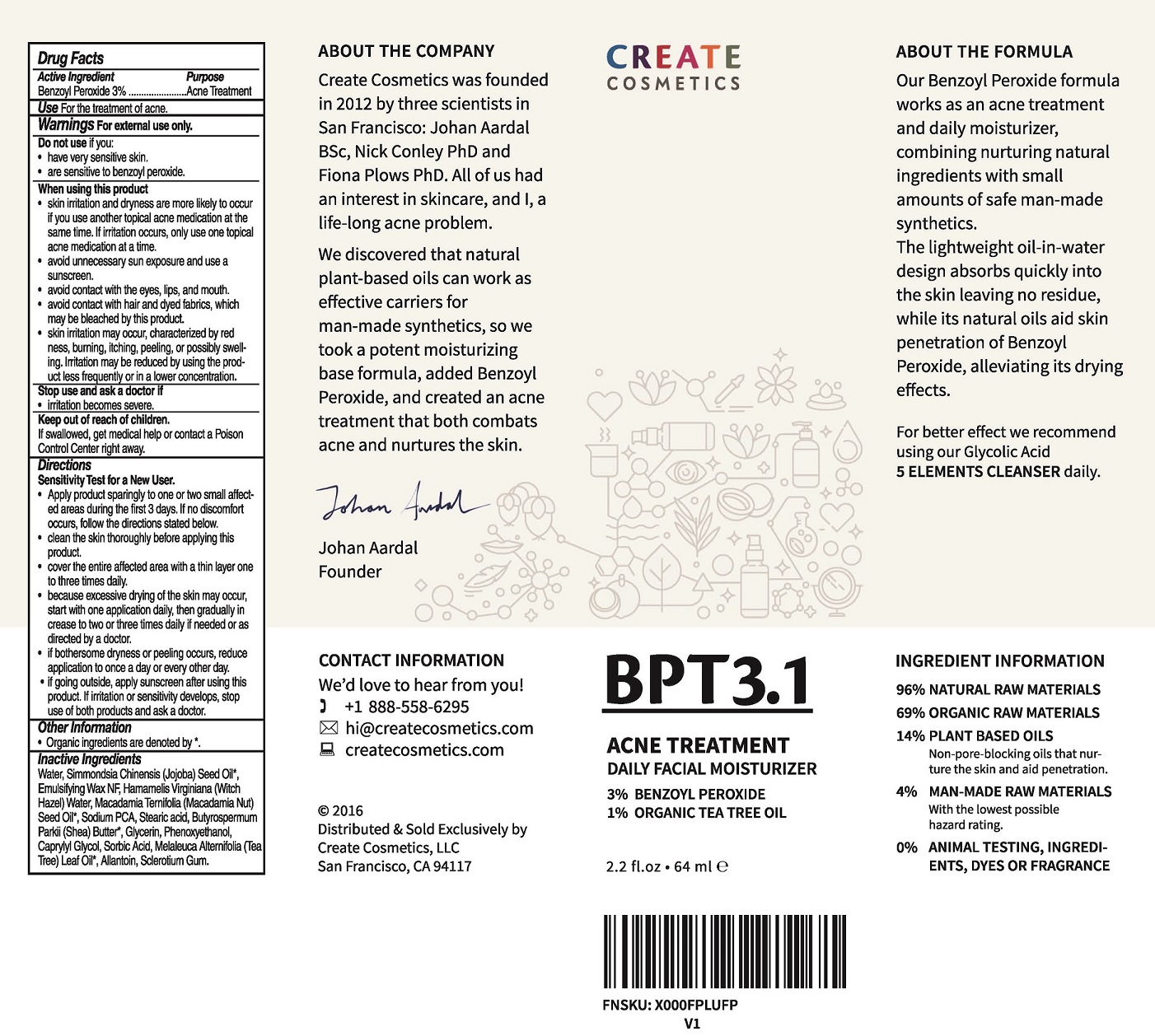 DRUG LABEL: BPT3.1 ACNE TREATMENT
NDC: 70162-102 | Form: LOTION
Manufacturer: Create Cosmetics, LLC
Category: otc | Type: HUMAN OTC DRUG LABEL
Date: 20240107

ACTIVE INGREDIENTS: BENZOYL PEROXIDE 3 g/100 mL
INACTIVE INGREDIENTS: WATER; JOJOBA OIL; CETOSTEARYL ALCOHOL; POLYSORBATE 60; WITCH HAZEL; MACADAMIA OIL; SODIUM PYRROLIDONE CARBOXYLATE; STEARIC ACID; SHEA BUTTER; GLYCERIN; PHENOXYETHANOL; CAPRYLYL GLYCOL; SORBIC ACID; TEA TREE OIL; ALLANTOIN; BETASIZOFIRAN

CREATE COSMETICS - BPT3.1 ACNE TREATMENT (70162-102)

ACTIVE INGREDIENT

BENZOYL PEROXIDE 3%

PURPOSE

ACNE TREATMENT

USE

FOR THE TREATMENT OF ACNE.

WARNINGS

FOR EXTERNAL USE ONLY

DO NOT USE IF YOU:

- HAVE VERY SENSITIVE SKIN.
- ARE SENSITIVE TO BENZOYL PEROXIDE.

WHEN USING THIS PRODUCT

- SKIN IRRITATION AND DRYNESS IS MORE LIKELY TO OCCUR IF YOU USE ANOTHER TOPICAL ACNE MEDICATION AT THE SAME TIME. IF IRRITATION OCCURS, ONLY USE ONE TOPICAL ACNE MEDICATION AT A TIME.
- AVOID UNNECESSARY SUN EXPOSURE AND USE A SUNSCREEN.
- AVOID CONTACT WITH THE EYES, LIPS, AND MOUTH.
- AVOID CONTACT WITH HAIR AND DYED FABRICS, WHICH MAY BE BLEACHED BY THIS PRODUCT.
- SKIN IRRITATION MAY OCCUR, CHARACTERIZED BY REDNESS, BURNING, ITCHING, PEELING, OR POSSIBLY SWELLING. IRRITATION MAY BE REDUCED BY USING THE PRODUCT LESS FREQUENTLY OR IN A LOWER CONCENTRATION.

STOP USE AND ASK A DOCTOR IF

- IRRITATION BECOMES SEVERE.

KEEP OUT OF REACH OF CHILDREN. IF SWALLOWED, GET MEDICAL HELP OR CONTACT A POISON CONTROL CENTER RIGHT AWAY.

DIRECTIONS

SENSITIVITY TEST FOR A NEW USER.
• APPLY PRODUCT SPARINGLY TO ONE OR TWO SMALL AFFECTED AREAS DURING THE FIRST 3 DAYS. IF NO DISCOMFORT OCCURS, FOLLOW THE DIRECTIONS STATED BELOW.
• CLEAN THE SKIN THOROUGHLY BEFORE APPLYING THIS PRODUCT.
• COVER THE ENTIRE AFFECTED AREA WITH A THIN LAYER ONE TO THREE TIMES DAILY.
• BECAUSE EXCESSIVE DRYING OF THE SKIN MAY OCCUR, START WITH ONE APPLICATION DAILY, THEN GRADUALLY INCREASE TO TWO OR THREE TIMES DAILY IF NEEDED OR AS DIRECTED BY A DOCTOR.
• IF BOTHERSOME DRYNESS OR PEELING OCCURS, REDUCE APPLICATION TO ONCE A DAY OR EVERY OTHER DAY.
• IF GOING OUTSIDE, APPLY SUNSCREEN AFTER USING THIS PRODUCT. IF IRRITATION OR SENSITIVITY DEVELOPS, STOP USE OF BOTH PRODUCTS AND ASK A DOCTOR.

OTHER INFORMATION

- ORGANIC INGREDIENTS ARE DENOTED WITH THE *.

INACTIVE INGREDIENTS

WATER, SIMMONDSIA CHINENSIS (JOJOBA) SEED OIL*, EMULSIFYING WAX NF, HAMAMELIS VIRGINIANA (WITCH HAZEL) WATER, MACADAMIA TERNIFOLIA (MACADAMIA NUT) SEED OIL*, SODIUM PCA, STEARIC ACID, BUTYROSPERMUM PARKII (SHEA) BUTTER*, GLYCERIN, PHENOXYETHANOL, CAPRYLYL GLYCOL, SORBIC ACID, MELALEUCA ALTERNIFOLIA (TEA TREE) LEAF OIL*, ALLANTOIN, SCLEROTIUM GUM.